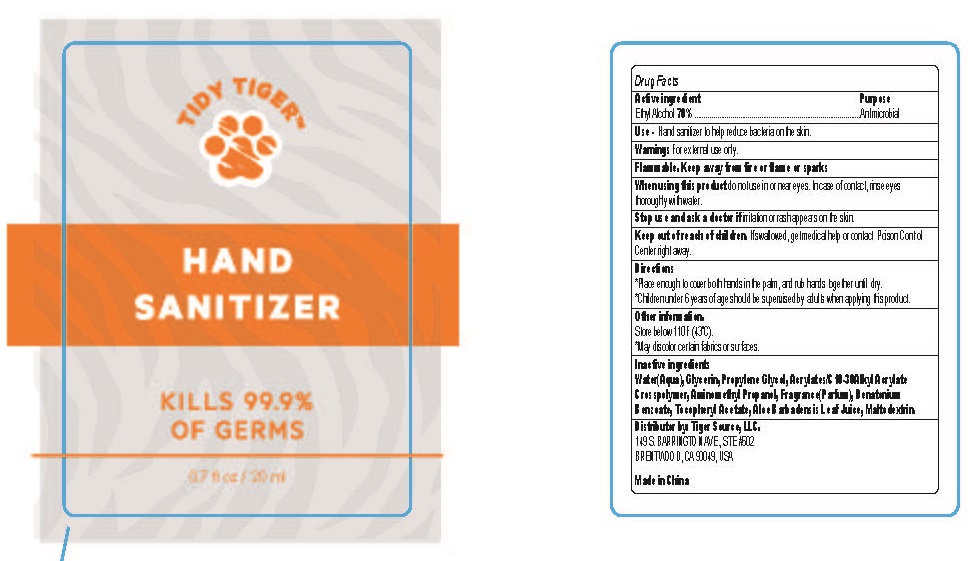 DRUG LABEL: TIDY TIGER Hand Sanitizer
NDC: 80273-007 | Form: SPRAY
Manufacturer: Tiger Source LLC
Category: otc | Type: HUMAN OTC DRUG LABEL
Date: 20200828

ACTIVE INGREDIENTS: ALCOHOL 70 mL/100 mL
INACTIVE INGREDIENTS: CARBOMER COPOLYMER TYPE A (ALLYL PENTAERYTHRITOL CROSSLINKED); AMINOMETHYLPROPANOL; .ALPHA.-TOCOPHEROL ACETATE; DENATONIUM BENZOATE; MALTODEXTRIN; ALOE VERA LEAF; WATER; GLYCERIN; PROPYLENE GLYCOL

TIDY TIGER™
HAND SANITIZER

Active ingredient

Ethyl Alcohol 70%

Purpose

Antimicrobial

Use

Hand sanitizer to help reduce bacteria on the skin.

Warnings

For external use only.

When using this product do not use in or near eyes. In case of contact, rinse eyes thoroughly with water.

Stop use and ask a doctor if irritation or rash appears on the skin.

Keep out of reach of children. If swallowed, get medical help or contact Poison Control Center right away.

Directions

- Place enough to cover both hands in the palm, and rub hands together until dry.
- Children under 6 years of age should be supervised by adults when applying this product.

Other information

Store below 110F (43C).

May discolor certain fabrics or surfaces.

Inactive ingredients:

Water(Aqua), Glycerin, Propylene Glycol, Acrylates/C10-30Alkyl Acrylate Crosspolymer, Aminomethyl Propanol, Fragrance(Parfum), Denatonium Benzoate, Tocopheryl Acetate, Aloe Barbadensis Leaf Juice, Maltodextrin.